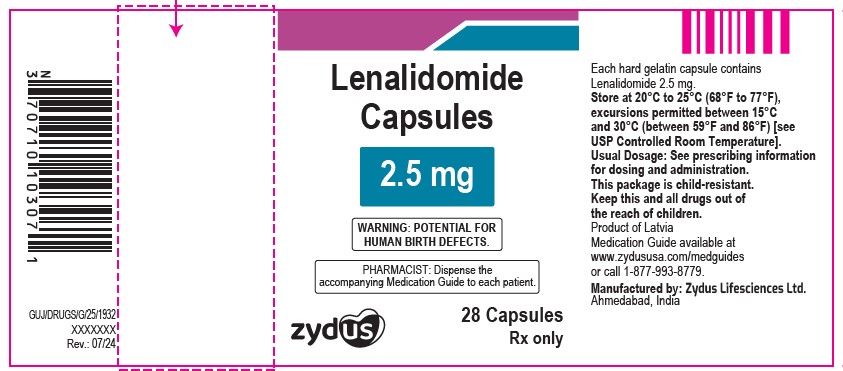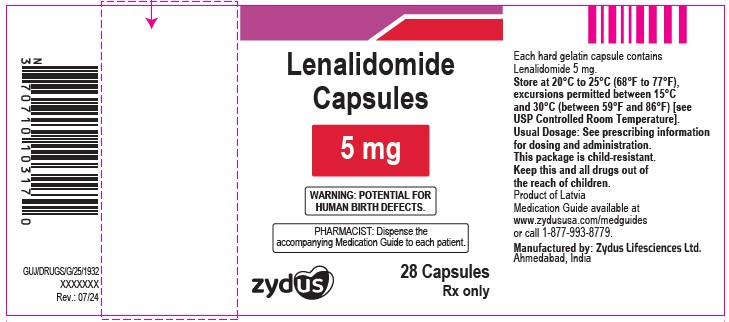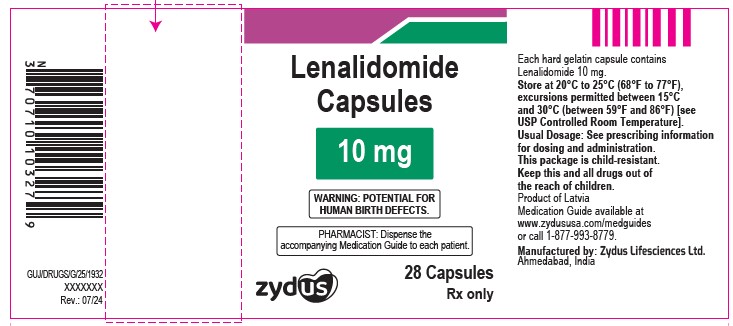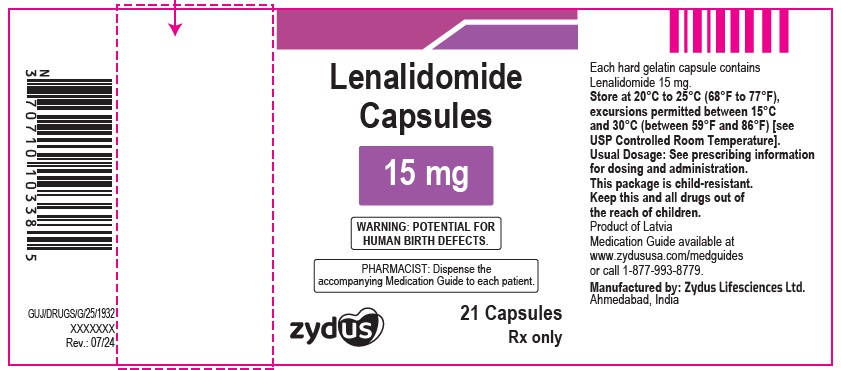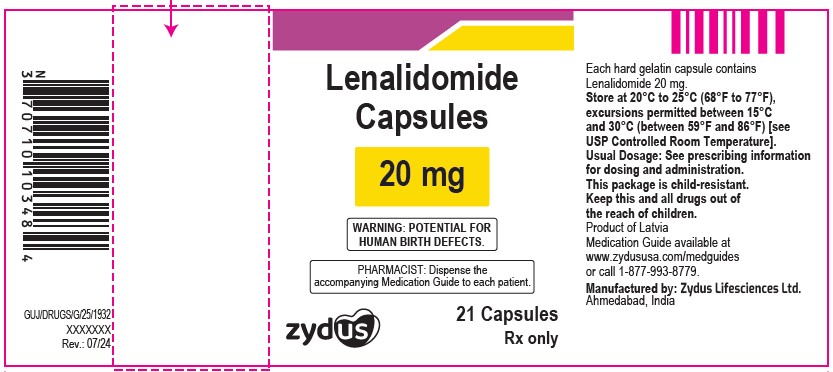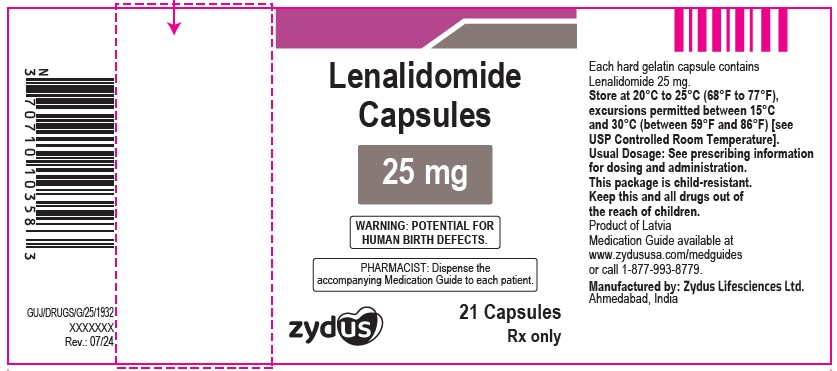 DRUG LABEL: LENALIDOMIDE
NDC: 70771-1677 | Form: CAPSULE
Manufacturer: Zydus Lifesciences Limited
Category: prescription | Type: HUMAN PRESCRIPTION DRUG LABEL
Date: 20241130

ACTIVE INGREDIENTS: LENALIDOMIDE 5 mg/1 1
INACTIVE INGREDIENTS: ANHYDROUS LACTOSE; CELLULOSE, MICROCRYSTALLINE; CROSCARMELLOSE SODIUM; FERROSOFERRIC OXIDE; GELATIN; LACTOSE MONOHYDRATE; MAGNESIUM STEARATE; POTASSIUM HYDROXIDE; SHELLAC; TITANIUM DIOXIDE

LENALIDOMIDE capsules, for oral use

PACKAGE LABEL.PRINCIPAL DISPLAY PANEL

NDC 70771-1676-7

Lenalidomide Capsules, 2.5 mg

28 Capsules

Rx only

NDC 70771-1677-7

Lenalidomide Capsules, 5 mg

28 Capsules

Rx only

NDC 70771-1678-7

Lenalidomide Capsules, 10 mg

28 Capsules

Rx only

NDC 70771-1679-8

Lenalidomide Capsules, 15 mg

21 Capsules

Rx only

NDC 70771-1680-8

Lenalidomide Capsules, 20 mg

21 Capsules

Rx only

NDC 70771-1681-8

Lenalidomide Capsules, 25 mg

21 Capsules

Rx only